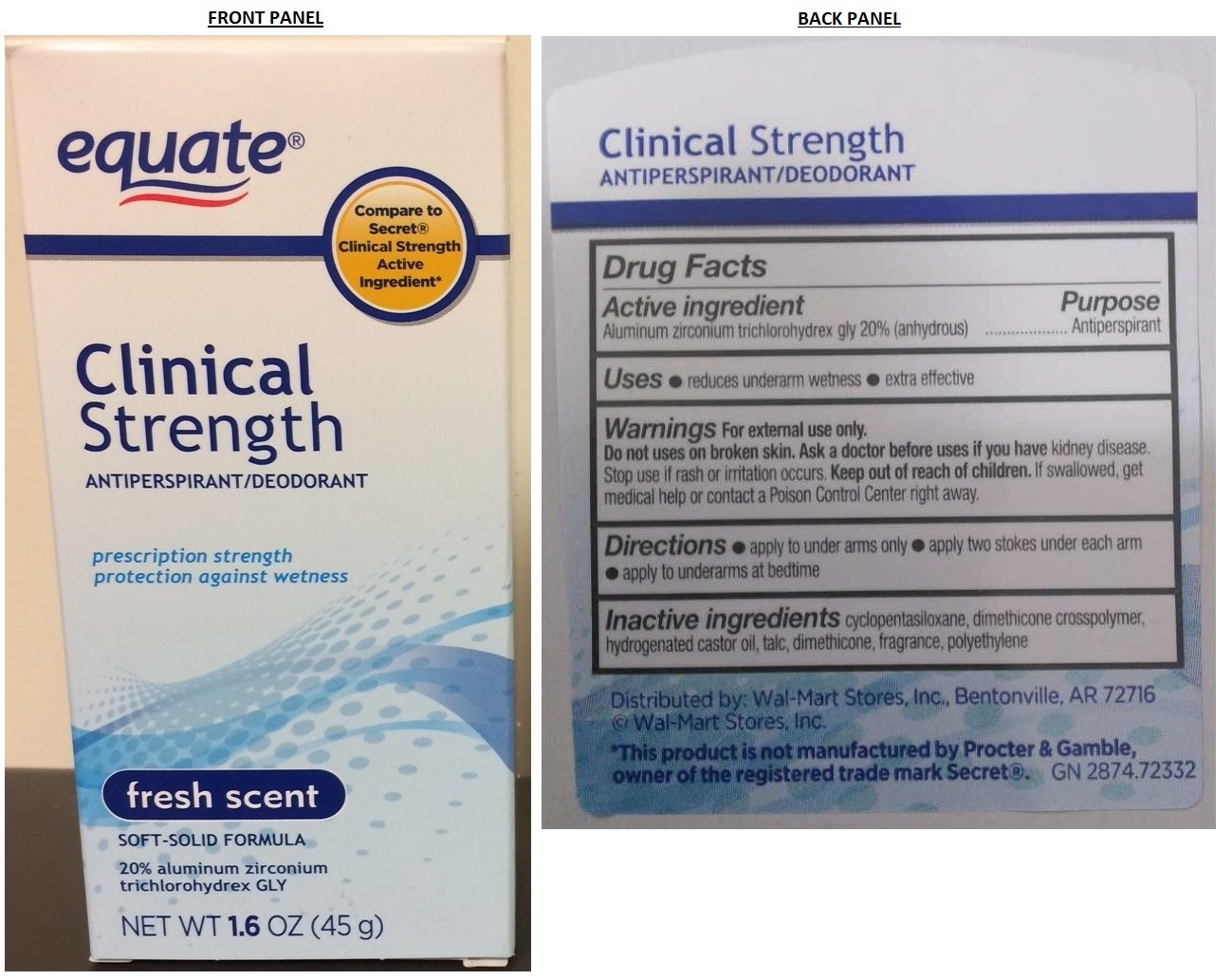 DRUG LABEL: equate Clinical Strength Antiperspirant/Deodorant
NDC: 49035-143 | Form: STICK
Manufacturer: Wal-mart Stores, Inc.
Category: otc | Type: HUMAN OTC DRUG LABEL
Date: 20170919

ACTIVE INGREDIENTS: ALUMINUM ZIRCONIUM TRICHLOROHYDREX GLY 0.2 g/1 g
INACTIVE INGREDIENTS: CYCLOMETHICONE 5; DIMETHICONE CROSSPOLYMER (450000 MPA.S AT 12% IN CYCLOPENTASILOXANE); HYDROGENATED CASTOR OIL; TALC; DIMETHICONE; LOW DENSITY POLYETHYLENE

equate Clinical Strength ANTIPERSPIRANT/DEODORANT

Active Ingredient

Aluminum zirconium trichlorohydrex gly 20% (anhydrous)

Purpose

Antiperspirant

Uses

• reduces underarm wetness • extra effective

Warnings

For external use only.

Do not use on broken skin. Ask a doctor before use if you have kidney disease. Stop use if rash or irritation occurs.

Keep out of reach of children. If swallowed, get medical help or contact a Poison Control Center right away.

Directions

• apply to underarms only • apply two strokes under each arm • apply to underarms at bedtime

Inactive ingredients

cyclopentasiloxane, dimethicone crosspolymer, hydrogenated castor oil, talc, dimethicone, fragrance, polyethylene

Questions?

1-888-287-1915

Compare to Secret® Clinical Strength Active Ingredient*

prescription strength protection against wetness

fresh scent

SOFT - SOLID FORMULA

Who benefits from using Equate® Clinical Strength Antiperspirant/Deodorant?

Anyone that currently suffers from excessive underarm perspiration will truly love the wetness protection of our product.

Satisfaction guaranteed- Or We'll replace it or give you your money back.

For questions or comments or to report an undesired reaction or side effects, please call 1-888-287-1915.

Distributed by: Wal-Mart Stores, Inc., Bentonville, AR 72716 © Wal-Mart Stores, Inc.

*This product is not manufactured by Procter & Gamble, owner of the registered trade mark Secret®. GN 2874.72332